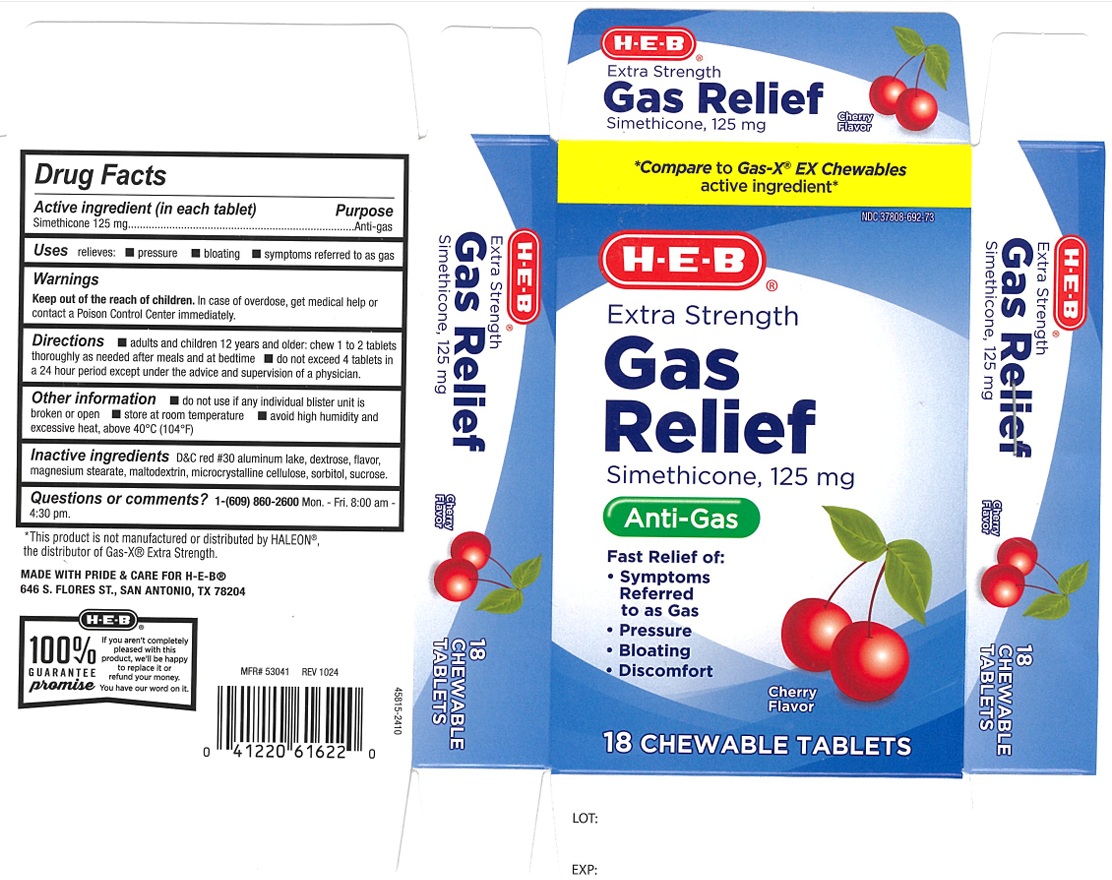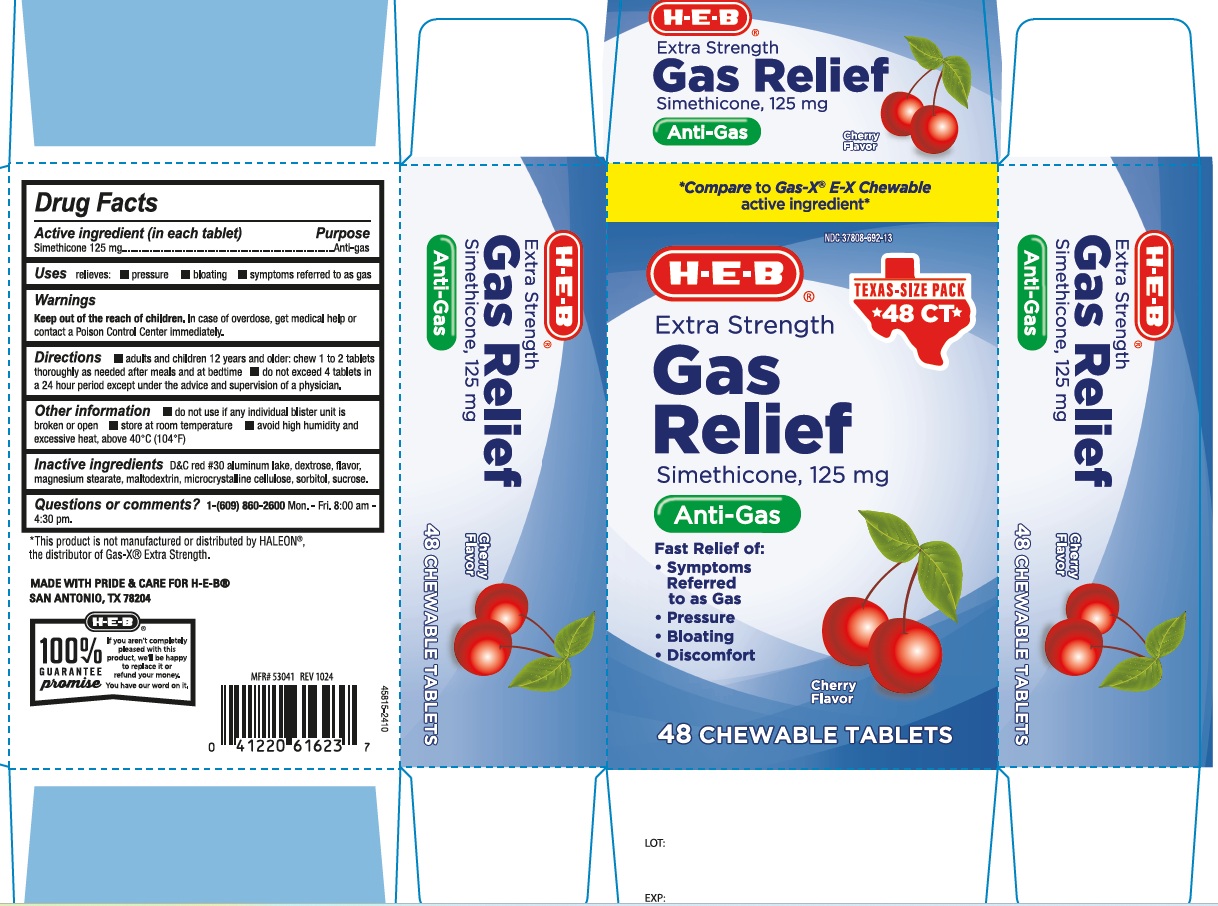 DRUG LABEL: Extra Strength Gas Relief Cherry
NDC: 37808-692 | Form: TABLET, CHEWABLE
Manufacturer: H E B
Category: otc | Type: Human OTC Drug Label
Date: 20250206

ACTIVE INGREDIENTS: DIMETHICONE 125 mg/1 1
INACTIVE INGREDIENTS: D&C RED NO. 30 ALUMINUM LAKE; MAGNESIUM STEARATE; CELLULOSE, MICROCRYSTALLINE; SORBITOL; SUCROSE; MALTODEXTRIN; DEXTROSE, UNSPECIFIED FORM

Extra Strength Gas Relief Cherry

ACTIVE INGREDIENT(in each tablet)

Simethicone 125 mg

PURPOSE

Anti-gas

USE(S)

relieves:

- pressure
- bloating
- symptoms referred to as gas

WARNINGS

.

KEEP OUT OF REACH OF CHILDREN

In case of overdose, get medical help or contact a Poison Control Center immediately.

DIRECTIONS

- adults and children 12 years and older: chew 1 to 2 tablets thoroughly as needed after meals and at bedtime
- do not exceed 4 tablets in a 24 hour period except under the advice and supervision of a physician.

OTHER INFORMATION

- do not use if any individual blister unit is broken or open
- store at room temperature
- avoid high humidity and excessive heat, above 40ºC (104ºF)

INACTIVE INGREDIENTS

D&C red # 30 aluminum lake, dextrose, flavor, magnesium stearate, maltodextrin, microcrystalline cellulose, sorbitol, sucrose.

PRINCIPAL DISPLAY PANEL

*Compare to Gas-X EX Chewables active ingredient*

NDC 37808-692-73

H-E-B

Extra Strength

Gas Relief

Simethicone, 125 mg

Antigas

Fast Relief of:

- symptoms Referred to as Gas
- Pressure
- Bloating
- Discomfort

Cherry Flavor

18 CHEWABLE TABLETS

*Compare to Gas-X EX Chewables active ingredient*

NDC 37808-692-13

H-E-B

Extra Strength

Gas Relief

Simethicone, 125 mg

Antigas

Fast Relief of:

- symptoms Referred to as Gas
- Pressure
- Bloating
- Discomfort

Cherry Flavor

48 CHEWABLE TABLETS